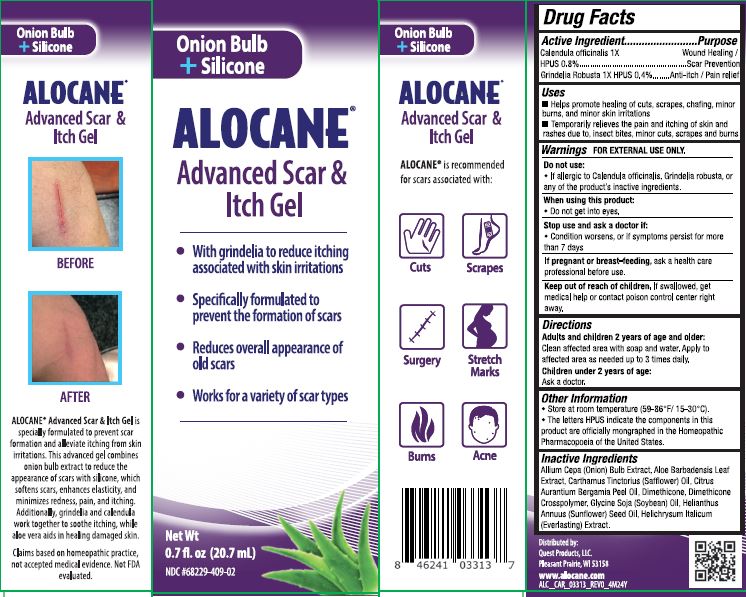 DRUG LABEL: Alocane Advanced Scar and Itch
NDC: 68229-409 | Form: GEL
Manufacturer: Quest Products, LLC
Category: homeopathic | Type: HUMAN OTC DRUG LABEL
Date: 20241105

ACTIVE INGREDIENTS: GRINDELIA HIRSUTULA FLOWERING TOP 1 [hp_X]/20.7 mL; CALENDULA OFFICINALIS FLOWER 1 [hp_X]/20.7 mL
INACTIVE INGREDIENTS: CARTHAMUS TINCTORIUS (SAFFLOWER) OLEOSOMES; ALOE BARBADENSIS LEAF EXTRACT; DIMETHICONE; CITRUS AURANTIUM BERGAMIA (BERGAMOT) PEEL OIL; HELIANTHUS ANNUUS (SUNFLOWER) SEED OIL; DIMETHICONE CROSSPOLYMER; GLYCINE SOJA (SOYBEAN) OIL; ONION; GAMOCHAETA PURPUREA FLOWER

Alocane Advanced Scar & Itch Gel

Active Ingredients

Calendula officinalis 1X HPUS 0.8%

Grindelia Robusta 1X HPUS 0.4%

Purpose

Wound Healing / Scar Prevention

Anti-itch / Pain relief

Uses

- Helps promote healing of cuts, scrapes, chafing, minor burns, and minor skin irritations
- Temprarily relieves the pain and itching of skin and rashes due to insect bites, minor cuts, scrapes and burns

Warnings

FOR EXTERNAL USE ONLY

Do not use if you are allergic to Calendula officinalis, Grindelia robusta, or any of the product's inactive ingredients.

When using this product:

- Do not get into eyes.

Stop use and ask a doctor if:

- Condition worsens, or if symptoms persist for more than 7 days.

If pregnant or breast-feeding,

ask a health care professional before use.

Keep out of reach of children.

If swallowed, get medical help or contact a poison control center right away.

Directions

Adults and children 2 years of age and older: Clean affected area with soap and water. Apply to affected area as needed up to 3 times daily.

Children under 2 years of age: Ask a doctor.

Other Information

- Store at room temperature (59-86^0F / 15-30^0C)
- The letters HPUS indicate the components in this product are officially monographed in the Homeopathic Pharmacopoeia of the United States.

Inactive Ingredients

Allum Cepa (onion) Bulb Extract, Aloe Barbadensis Leaf Extract, Carthamus Tinctorius (Safflower) Oil, Citrus Aurantium Bergamia Peel Oil, Dimethicone, Dimethicone Crosspolymer, Glycine Soja (Soybean) Oil, Helianthus Annuus (Sunflower) Seed Oil, Helchrysum Italicum (Everlasting) Extract.